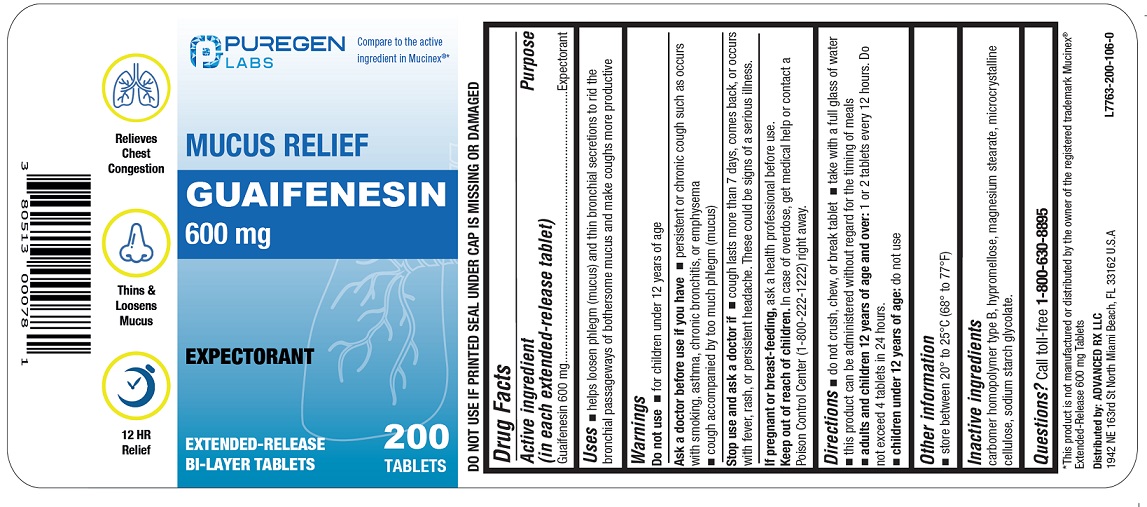 DRUG LABEL: Mucus Relief
NDC: 80513-403 | Form: TABLET, EXTENDED RELEASE
Manufacturer: Advanced Rx LLC
Category: otc | Type: HUMAN OTC DRUG LABEL
Date: 20240829

ACTIVE INGREDIENTS: GUAIFENESIN 600 mg/1 1
INACTIVE INGREDIENTS: CARBOMER HOMOPOLYMER TYPE B (ALLYL PENTAERYTHRITOL CROSSLINKED); HYPROMELLOSE, UNSPECIFIED; SODIUM STARCH GLYCOLATE TYPE A; MAGNESIUM STEARATE; MICROCRYSTALLINE CELLULOSE

Drug Facts

Active ingredient (in each extended-release tablet)

Guaifenesin 600 mg

Purpose

Expectorant

Uses

■ helps loosen phlegm (mucus) and thin bronchial secretions to rid the bronchial passageways of bothersome mucus and make coughs more productive

Warnings

Do not use

■ for children under 12 years of age

Ask a doctor before use if you have

■ persistent or chronic cough such as occurs with smoking, asthma, chronic bronchitis, or emphysema

■ cough accompanied by too much phlegm (mucus)

Stop use and ask a doctor if

■ cough lasts more than 7 days, comes back, or occurs with fever, rash, or persistent headache. These could be signs of a serious illness.

PREGNANCY OR BREAST FEEDING

If pregnant or breast-feeding, ask a health professional before use.

Keep out of reach of children.In case of overdose, get medical help or contact a Poison Control Center (1-800-222-1222) right away.

Directions

■ do not crush, chew, or break tablet

■ take with a full glass of water

■ this product can be administered without regard for the timing of meals

■ adults and children 12 years of age and over:1 or 2 tablets every 12 hours. Do not exceed 4 tablets in 24 hours.

■ children under 12 years of age:do not use

Other information

■ store between 20º to 25ºC (68º to 77ºF)

■ DO NOT USE IF PRINTED SEAL UNDER CAP IS MISSING OR DAMAGED

Inactive ingredients

carbomer homopolymer type B, hypromellose, magnesium stearate, microcrystalline cellulose, sodium starch glycolate.

Questions?

Call toll-free 1-800-630-8895

Distributed by:

ADVANCED RX LLC

1942 NE 163rd St North Miami Beach,

FL 33162 U.S.A

PRINCIPAL DISPLAY PANEL

NDC 80513-403-20

*Compare to the active ingredient in Mucinex®

Mucus Relief

Guaifenesin 600 mg

Expectorant

EXTENDED-RELEASE TABLETS BI-LAYER TABLETS

200 Tablets

*This product is not manufactured or distributed by the owner of the registered trademark Mucinex®Extended-Release 600 mg Tablets